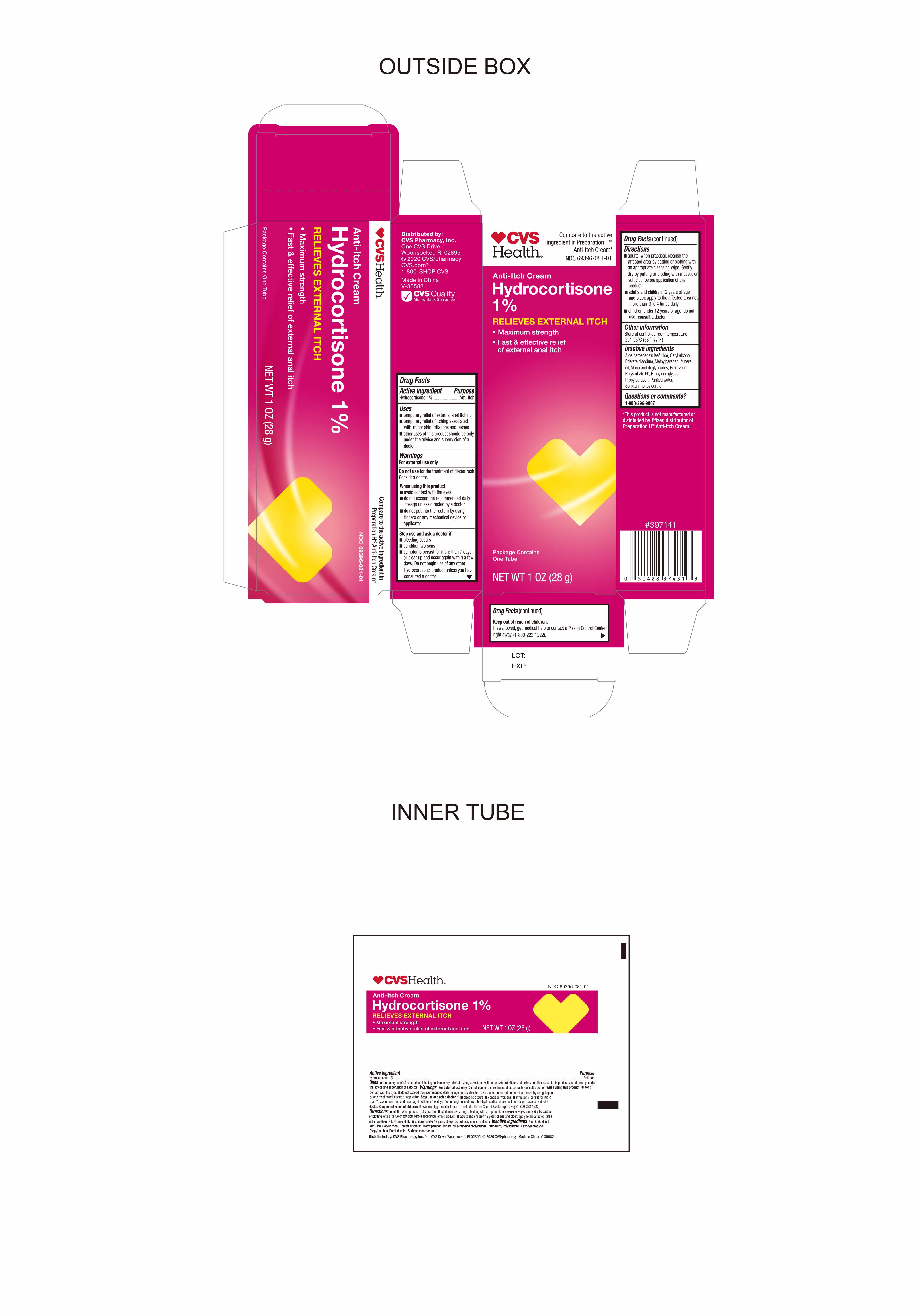 DRUG LABEL: Hydrocortisone 1%
NDC: 69396-081 | Form: CREAM
Manufacturer: Trifecta Pharmaceuticals Usa Llc
Category: otc | Type: HUMAN OTC DRUG LABEL
Date: 20241218

ACTIVE INGREDIENTS: HYDROCORTISONE 1 g/100 g
INACTIVE INGREDIENTS: GLYCERYL MONO AND DIPALMITOSTEARATE; PROPYLPARABEN; MINERAL OIL; EDETATE DISODIUM; PROPYLENE GLYCOL; SORBITAN MONOSTEARATE; METHYLPARABEN; POLYSORBATE 60; ALOE VERA LEAF; CETYL ALCOHOL; PETROLATUM; WATER

CVS Anti-Itch Cream Hydrocortisone 1%

Active ingredient

Hydrocortisone 1%

Purpose

Anti-Itch

Uses

temporary relieves external anal itching.

temporary relief of itching associated with minor skin irritations and rashes

other uses of this product should be only under the advice and supervision of a doctor

When Using this Product

Avoid Contact with eyes

do not exceed the recommended daily dosage unless directed by a doctor

do not put into the rectum by using fingers or any mechanical device or applicator

Warnings

for external use only

Directions

●Adults when practical, cleanse the affected area by patting or blotting with an appropriate cleansing wipe.

●gently dry by patting or blotting with a tissue or soft cloth before application of this product.

●adults and children 12 years of age and older: apply to the affected area not more than 3 to 4 times daily.

●children under 12 years of age: do not use, consult a doctor.

Inactive ingredients

Aloe barbadensis leaf juice, ethylparaben, glycerin, glycerol monostearate, hexadecanol, mineral water, octadecanol, petrolatum, purified water, sodium dodecyl sulfate

Other information

● store at controlled room temperature 20°-25°C (68 °- 77 °F)

Keep out of Reach of Children

If swallowed, get medical help or contact Poison Control Center right away (1-800-222-1222)

Stop Use and Ask a Doctor if

bleeding occurs

condition worsens

symptoms persist for more than 7 days or clear up and occur again within a few days. Do not begin use of any other hydrocortisone product unless you have consulted a doctor.

Qustions or Comments

Call 1 800 296-9067

Do not use for the treatment of Diaper Rash. Consult Doctor.

Other Information

Distributed by:

CVS Pharmacy, Inc.

One CVS Drive

Woonsocket, RI 02895

© 2020 CVS Pharmacy

CVS.com

1 800 Shop CVS

Made in China

V-36582

This product is not manufactured or distributed by Pfizer, distributor of Preparation H Anti-itch Cream.